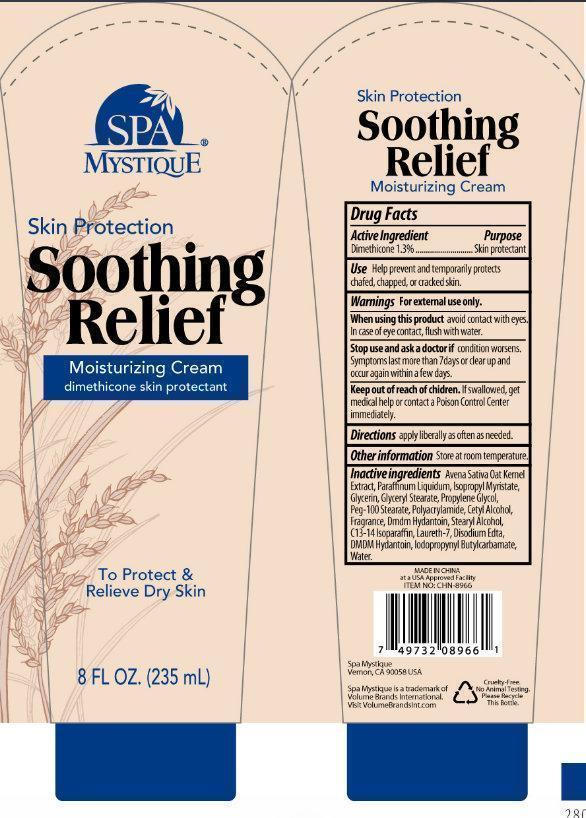 DRUG LABEL: SPA Mystique Skin Protection Soothing Relief Moisturizing
                
NDC: 50523-101 | Form: CREAM
Manufacturer: Volume Distributors, Inc.
Category: otc | Type: HUMAN OTC DRUG LABEL
Date: 20140804

ACTIVE INGREDIENTS: DIMETHICONE 13 mg/1 mL
INACTIVE INGREDIENTS: OAT; MINERAL OIL; ISOPROPYL MYRISTATE; GLYCERIN; GLYCERYL MONOSTEARATE; PROPYLENE GLYCOL; PEG-100 STEARATE; POLYACRYLAMIDE (10000 MW); CETYL ALCOHOL; DMDM HYDANTOIN; STEARYL ALCOHOL; C13-14 ISOPARAFFIN; LAURETH-7; EDETATE DISODIUM; IODOPROPYNYL BUTYLCARBAMATE; WATER

SPA Mystique Skin Protection Soothing Relief Moisturizing Cream

Active Ingredient

Dimethicone.............1.3%

Purpose

Skin protectant

Use

Help prevent and temporarily protects chafed, chapped, or cracked skin.

Warnings

For external use only.

When using this product

avoid contact with eyes. In case of eye contact, flush with water.

Stop use and ask a doctor if

condition worsens. Symptoms last more than 7 days or clear up and occur again within a few days.

Keep out of reach of children.

If swallowed, get medical help or contact a Poison Control Center immediately.

Directions

apply liberally as often as needed.

Other information

Store at room temperature.

Inactive ingredients

Avena Sativa Kernel Extract, Paraffinum Liquidum, Isopropyl Myristate, Glycerin, Glyceryl Stearate, Propylene Glycol, PEG-100 Stearate, Polyacrylamide, Cetyl Alcohol, Fragrance, DMDM Hydantoin, Stearyl Alcohol, C13-14 Isoparaffin, Laureth-7, Disodium EDTA, Iodopropynyl Butylcarbamate, Water